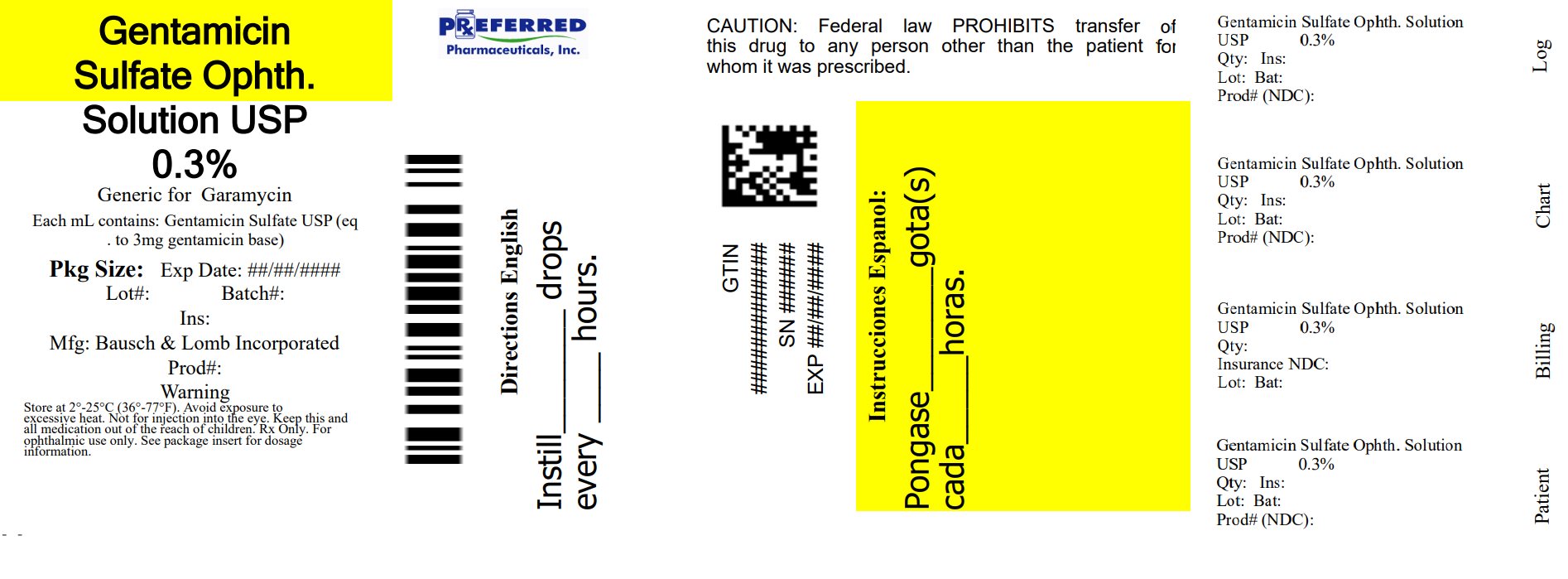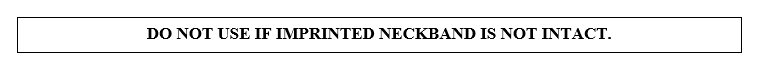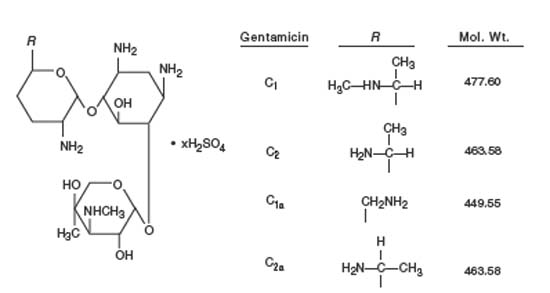 DRUG LABEL: Gentamicin Sulfate
NDC: 68788-8592 | Form: SOLUTION/ DROPS
Manufacturer: Preferred Pharmaceuticals Inc.
Category: prescription | Type: HUMAN PRESCRIPTION DRUG LABEL
Date: 20250612

ACTIVE INGREDIENTS: GENTAMICIN SULFATE 3 mg/1 mL
INACTIVE INGREDIENTS: SODIUM CHLORIDE; SODIUM PHOSPHATE, MONOBASIC, UNSPECIFIED FORM; WATER; HYDROCHLORIC ACID; SODIUM HYDROXIDE; BENZALKONIUM CHLORIDE; SODIUM PHOSPHATE, DIBASIC, UNSPECIFIED FORM

Gentamicin Sulfate
Ophthalmic Solution, USP
0.3%
(Sterile)
Rx only

DESCRIPTION

Gentamicin sulfate ophthalmic solution, USP is a sterile, aqueous solution buffered to approximately pH 7.0 and formulated for ophthalmic use.

Each mL contains:

Active: gentamicin sulfate, USP (equivalent to 3 mg gentamicin).

Inactives: dibasic sodium phosphate, sodium chloride, monobasic sodium phosphate, purified water. Hydrochloric acid and/or sodium hydroxide may be added to adjust pH (6.5 - 7.5).

Preservative: benzalkonium chloride 0.01%.

Gentamicin is an aminoglycoside antibiotic obtained from cultures of Micromonospora purpurea. It is a mixture of the sulfate salts of gentamicin C1, C2, C1a and C2a. All three components appear to have similar antimicrobial activity. Gentamicin sulfate occurs as a white to buff powder and is soluble in water and insoluble in alcohol.

The structural formula is as follows:

CLINICAL PHARMACOLOGY

Microbiology

Gentamicin sulfate is active in vitro against many strains of the following microorganisms:

Staphylococcus aureus, Staphylococcus epidermidis, Streptococcus pyogenes, Streptococcus pneumoniae, Enterobacter aerogenes, Escherichia coli, Haemophilus influenzae, Klebsiella pneumoniae, Neisseria gonorrhoeae, Pseudomonas aeruginosa, and Serratia marcescens.

INDICATIONS AND USAGE

Gentamicin sulfate ophthalmic solution is indicated in the topical treatment of ocular bacterial infections including conjunctivitis, keratitis, keratoconjunctivitis, corneal ulcers, blepharitis, blepharoconjunctivitis, acute meibomianitis, and dacryocystitis, caused by susceptible strains of the following microorganisms:

Staphylococcus aureus, Staphylococcus epidermidis, Streptococcus pyogenes, Streptococcus pneumoniae, Enterobacter aerogenes, Escherichia coli, Haemophilus influenzae, Klebsiella pneumoniae, Neisseria gonorrhoeae, Pseudomonas aeruginosa, and Serratia marcescens.

CONTRAINDICATIONS

Gentamicin sulfate ophthalmic solution is contraindicated in patients with known hypersensitivity to any of its components.

WARNINGS

NOT FOR INJECTION INTO THE EYE

Gentamicin sulfate ophthalmic solution is not for injection. It should never be injected subconjunctivally, nor should it be directly introduced into the anterior chamber of the eye.

PRECAUTIONS

General

Prolonged use of topical antibiotics may give rise to overgrowth of nonsusceptible organisms including fungi. Bacterial resistance to gentamicin may also develop. If purulent discharge, inflammation or pain becomes aggravated, the patient should discontinue use of the medication and consult a physician. If irritation or hypersensitivity to any component of the drug develops, the patient should discontinue use of this preparation and appropriate therapy should be instituted.

Information for Patients

To avoid contamination, do not touch tip of container to the eye, eyelid or any surface.

Carcinogenesis, Mutagenesis, Impairment of Fertility

There are no published carcinogenicity or impairment of fertility studies on gentamicin. Aminoglycoside antibiotics have been found to be non-mutagenic.

Pregnancy

Gentamicin has been shown to depress body weights, kidney weights and median glomerular counts in newborn rats when administered systemically to pregnant rats in daily doses approximately 500 times the maximum recommended ophthalmic human dose. There are no adequate and well-controlled studies in pregnant women. Gentamicin should be used during pregnancy only if the potential benefit justifies the potential risk to the fetus.

ADVERSE REACTIONS

Bacterial and fungal corneal ulcers have developed during treatment with gentamicin ophthalmic preparations.

The most frequently reported adverse reactions are ocular burning and irritation upon drug instillation, non-specific conjunctivitis, conjunctival epithelial defects and conjunctival hyperemia.

Other adverse reactions which have occurred rarely are allergic reactions, thrombocytopenic purpura and hallucinations.

To report SUSPECTED ADVERSE REACTIONS, contact Bausch & Lomb Incorporated at 1-800-553-5340 or FDA at 1-800-FDA-1088 or www.fda.gov/medwatch.

DOSAGE AND ADMINISTRATION

Instill one or two drops into the affected eye(s) every four hours. In severe infections dosage may be increased to as much as two drops every hour.

HOW SUPPLIED

Gentamicin sulfate ophthalmic solution USP, 0.3% is supplied sterile in a white LDPE plastic bottle, with a white LLDPE extended controlled drop tip and white polypropylene cap in the following size:

NDC 68788-8592-5- 5 mL

NOT FOR INJECTION INTO THE EYE

FOR OPHTHALMIC USE ONLY

Storage: Store between 2°C to 25°C (36°F to 77°F). Avoid exposure to excessive heat.

KEEP OUT OF REACH OF CHILDREN.

Distributed by:
Bausch & Lomb Americas Inc.
Bridgewater, NJ 08807 USA
Manufactured by:
Bausch & Lomb Incorporated
Tampa, FL 33637 USA
© 2022 Bausch & Lomb Incorporated or its affiliates
Revised: September 2022

9116006 (Folded)

9116106 (Flat)

Relabeled By: Preferred Pharmaceuticals Inc.

PACKAGE/LABEL PRINCIPAL DISPLAY PANEL

NDC 68788-8592-5

Gentamicin
Sulfate
Ophthalmic
Solution, USP
0.3%
(Sterile)
FOR OPHTHALMIC
USE ONLY
Rx only
5 mL
BAUSCH + LOMB
9531302
AB07707

Relabeled By: Preferred Pharmaceuticals Inc.